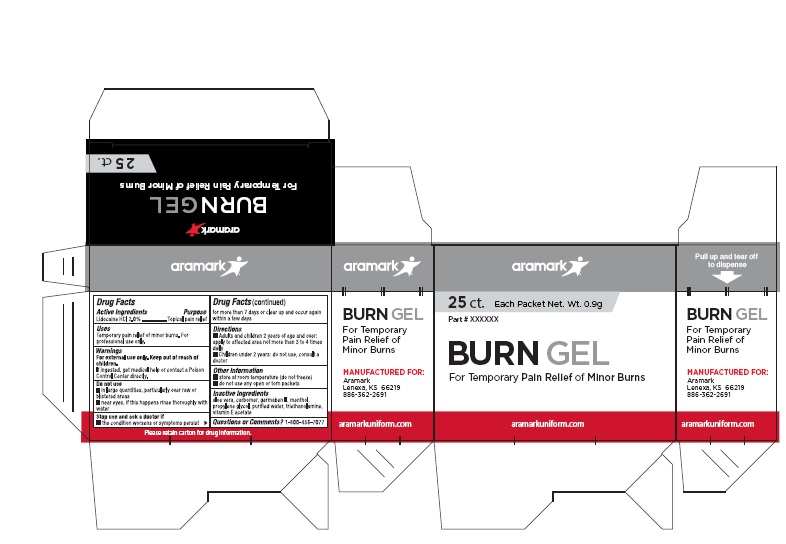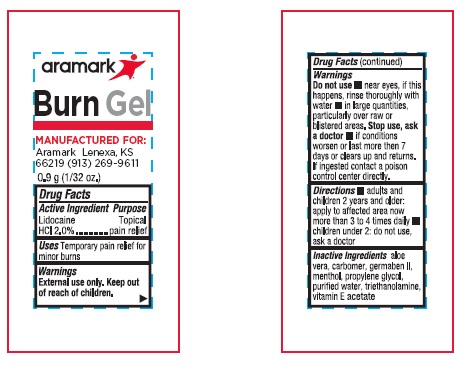 DRUG LABEL: Aramark Burn Gel
NDC: 81238-5000 | Form: GEL
Manufacturer: Western First Aid Safety DBA Aramark
Category: otc | Type: HUMAN OTC DRUG LABEL
Date: 20210909

ACTIVE INGREDIENTS: LIDOCAINE HYDROCHLORIDE 20 mg/1 g
INACTIVE INGREDIENTS: ALOE VERA LEAF; CARBOMER HOMOPOLYMER, UNSPECIFIED TYPE; DIAZOLIDINYL UREA; MENTHOL; PROPYLENE GLYCOL; WATER; TROLAMINE; .ALPHA.-TOCOPHEROL ACETATE

aramark Burn Gel

Drug Facts

Active Ingredients

Lidocaine HCL 2.0%

Purpose

Topical pain relief

Uses

Temporary pain relief for minor burns. For

professional use only.

Warnings

For external use only.

Keep out of reach of children.

If swallowed, get medical help or contact a Poison Control Center directly.

Do not use

- in large quantities, particularly over raw or blistered areas
- near eyes, if this happens rinse thoroughly with water

Stop use and ask a doctor if

• the condition worsens or symptoms persist for more

than 7 days or clear up and occur again within a few days

Directions

• Adults and children 2 years of age and older:

apply to affected area not more than 3 to 4 times daily

• Children under 2 years: do not use, consult a doctor

Other Information

• store at room temperature (do not freeze)

• do not use any open or torn packets

Inactive ingredients

aloe vera, carbomer, germaben II, menthol,

propylene glycol, purified water, triethanolamine,

vitamin E acetate

Questions od Comments?

1-800-456-7077

Package Labeling

aramark

25 ct. Each Packet Net. Wt. 0.9g

BURN GEL
For Temporary Pain Relief of Minor Burns

aramarkuniform.com

MANUFACTURED FOR:
Aramark
Lenexa, KS 66219

886-362-2691

Please retain carton for drug information.

res